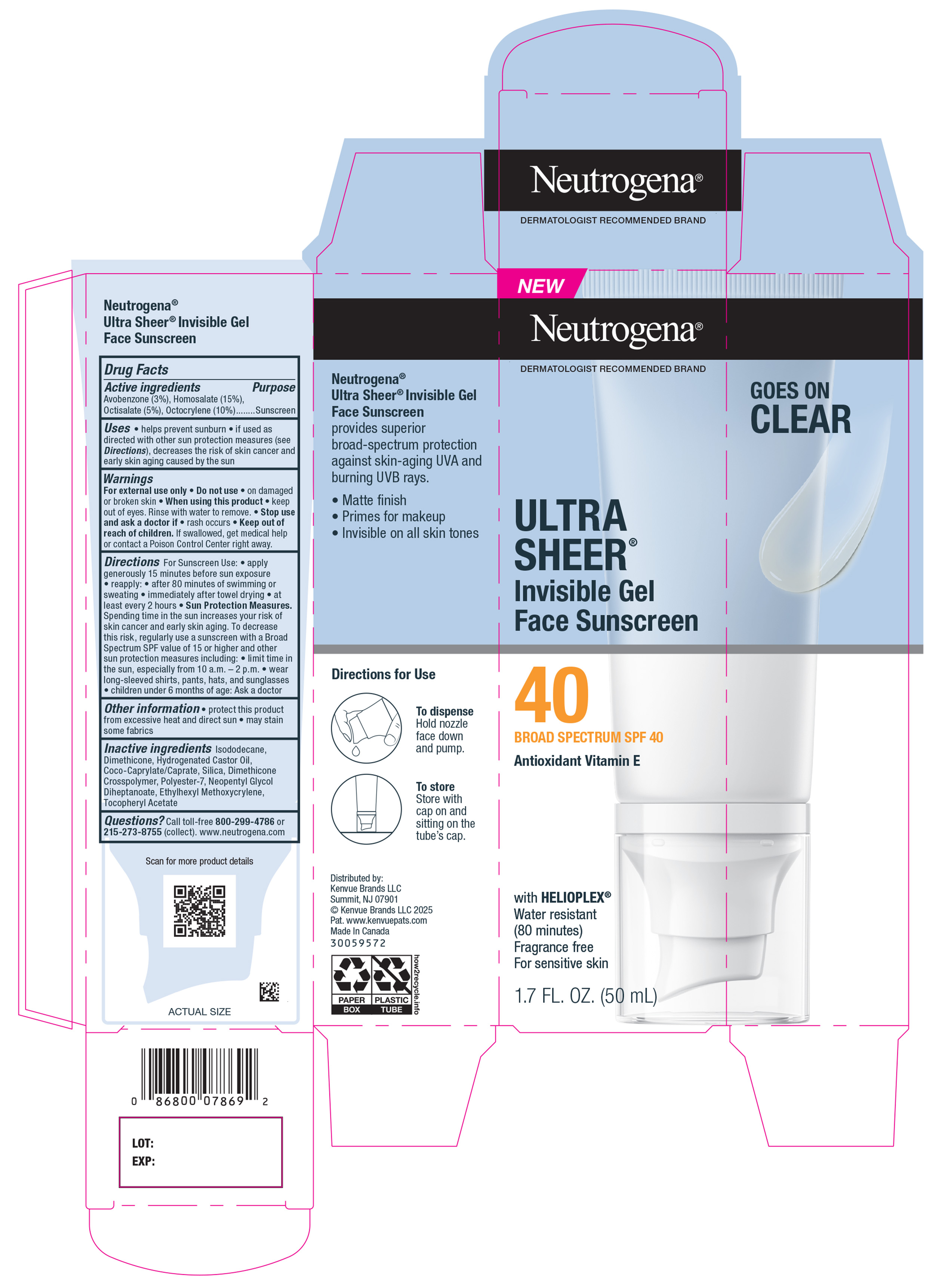 DRUG LABEL: Neutrogena Ultra Sheer Invisible Gel Face Sunscreen SPF 40 Broad Spectrum
NDC: 69968-0935 | Form: GEL
Manufacturer: Kenvue Brands LLC
Category: otc | Type: HUMAN OTC DRUG LABEL
Date: 20250805

ACTIVE INGREDIENTS: OCTISALATE 50 mg/1 mL; OCTOCRYLENE 100 mg/1 mL; AVOBENZONE 30 mg/1 mL; HOMOSALATE 150 mg/1 mL
INACTIVE INGREDIENTS: DIMETHICONE CROSSPOLYMER; SILICA; ETHYLHEXYL METHOXYCRYLENE; NEOPENTYL GLYCOL DIHEPTANOATE; HYDROGENATED CASTOR OIL; ISODODECANE; POLYESTER-7; DIMETHICONE; COCO-CAPRYLATE/CAPRATE; ALPHA-TOCOPHEROL ACETATE

Neutrogena Ultra Sheer Invisible Gel Face Sunscreen SPF 40 Broad Spectrum

Drug Facts

ACTIVE INGREDIENT

Avobenzone (3%),

Homosalate (15%),

Octisalate (5%),

Octocrylene (10%)

PURPOSE

Sunscreen

Uses

- helps prevent sunburn
- if used as directed with other sun protection measures (see Directions), decreases the risk of skin cancer and early skin aging caused by the sun

Warnings

For external use only

Do not use on damaged or broken skin

- When using this product keep out of eyes. Rinse with water to remove.

Stop use and ask a doctor if rash occurs

Keep out of reach of children. If swallowed, get medical help or contact a Poison Control Center right away

Directions

- For Sunscreen use: ● apply generously and evenly 15 minutes before sun exposure
- ● reapply: after 80 minutes of swimming or sweating ● immediately after towel drying ● at least every 2 hours ● Sun Protection Measures. Spending time in the sun increases your risk of skin cancer and early skin aging. To decrease this risk, regularly use a sunscreen with a Broad Spectrum SPF value of 15 or higher and other sun protection measures including: ● limit time in the sun, especially from 10 a.m. – 2 p.m. ● wear long-sleeved shirts, pants, hats, and sunglasses ● children under 6 months of age: Ask a doctor

Other information

- protect this product from excessive heat and direct sun
- May stain some fabrics

Inactive ingredients

Isododecane, Dimethicone, Hydrogenated Castor Oil, Coco-Caprylate/Caprate, Silica, Dimethicone Crosspolymer, Polyester-7, Neopentyl Glycol Diheptanoate, Ethylhexyl Methoxycrylene, Tocopheryl Acetate

Questions?

Call toll-free 800-299-4786 or 215-273-8755 (collect). www.neutrogena.com

Distributed by:

Kenvue Brands LLC
Summit, NJ 07901

PRINCIPAL DISPLAY PANEL - 50 mL Carton Label

NEW

Neutrogena®

DERMATOLOGIST RECOMMENDED BRAND

ULTRA

SHEER®

Invisible Gel

Face Sunscreen

40

BROAD SPECTRUM SPF 40

Antioxidant Vitamin E

with HELIOPLEX®

Water resistant

(80 minutes)

Fragrance free

For sensitive skin

1.7 FL. OZ. (50 mL)